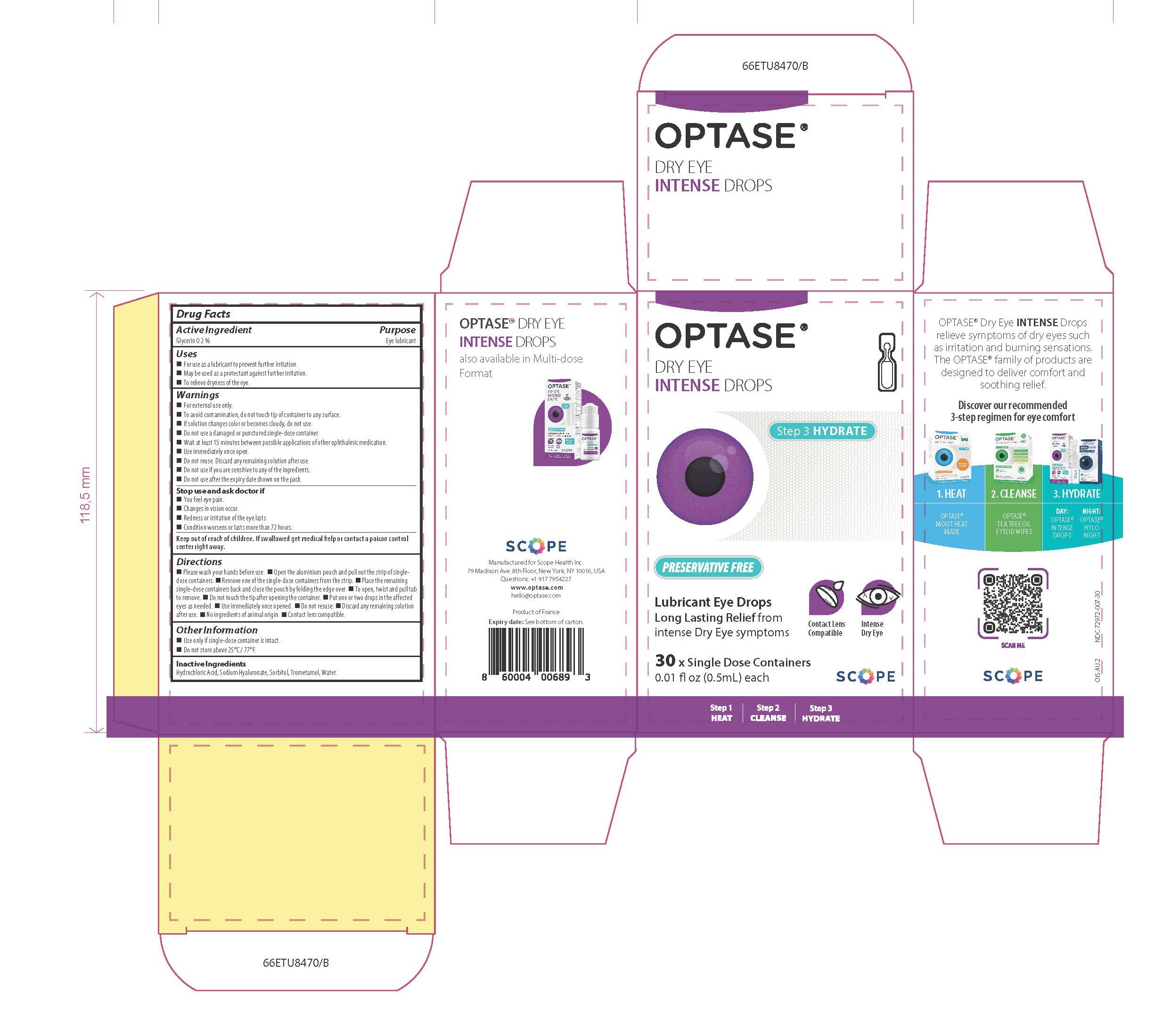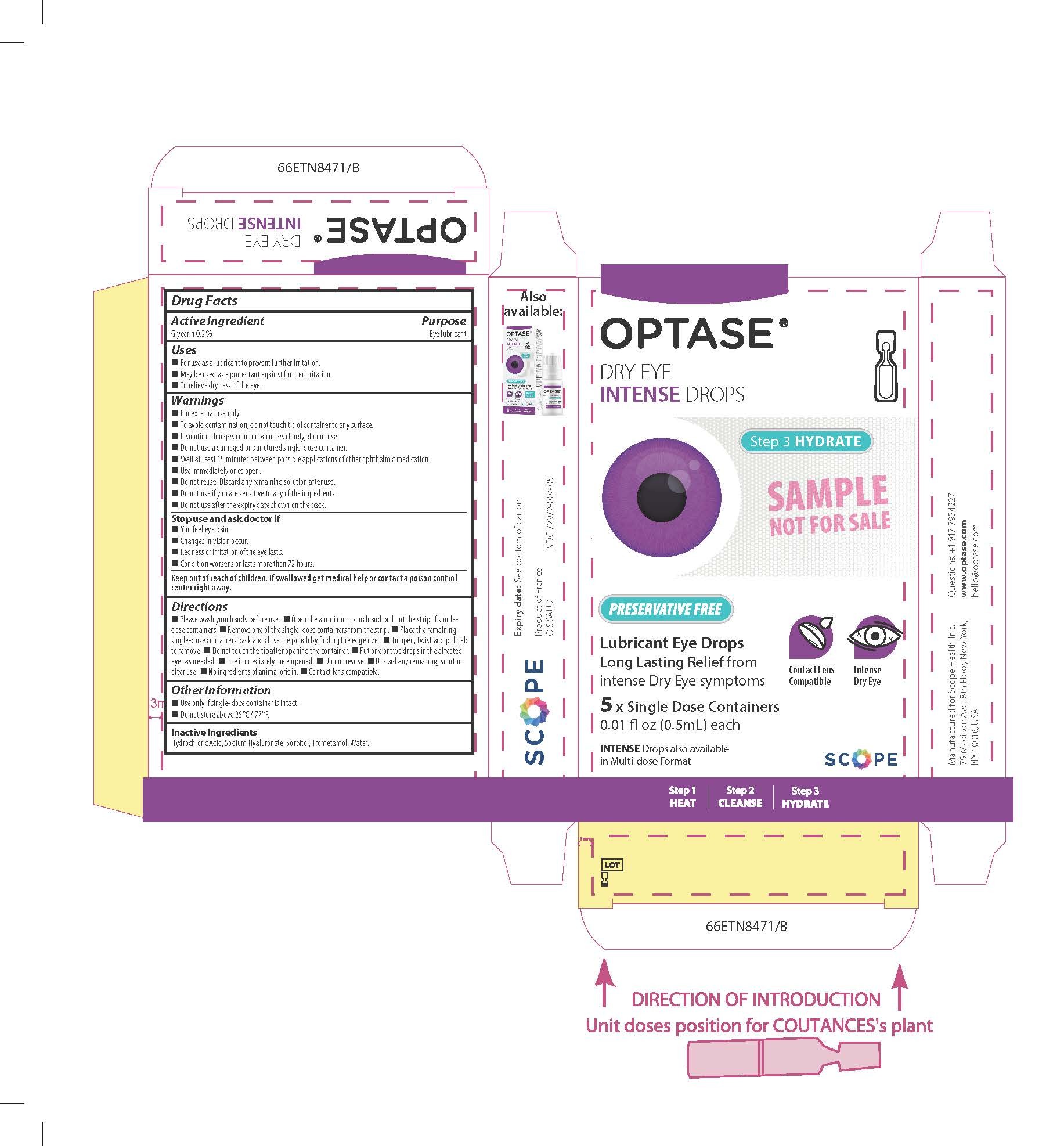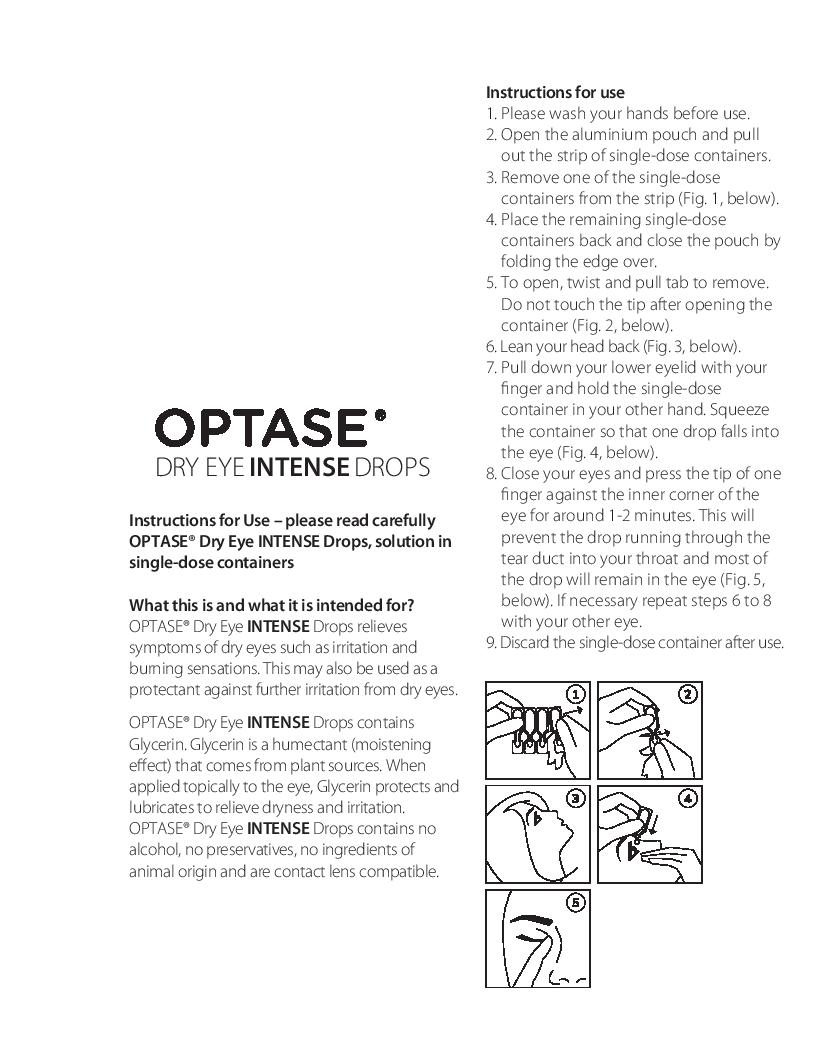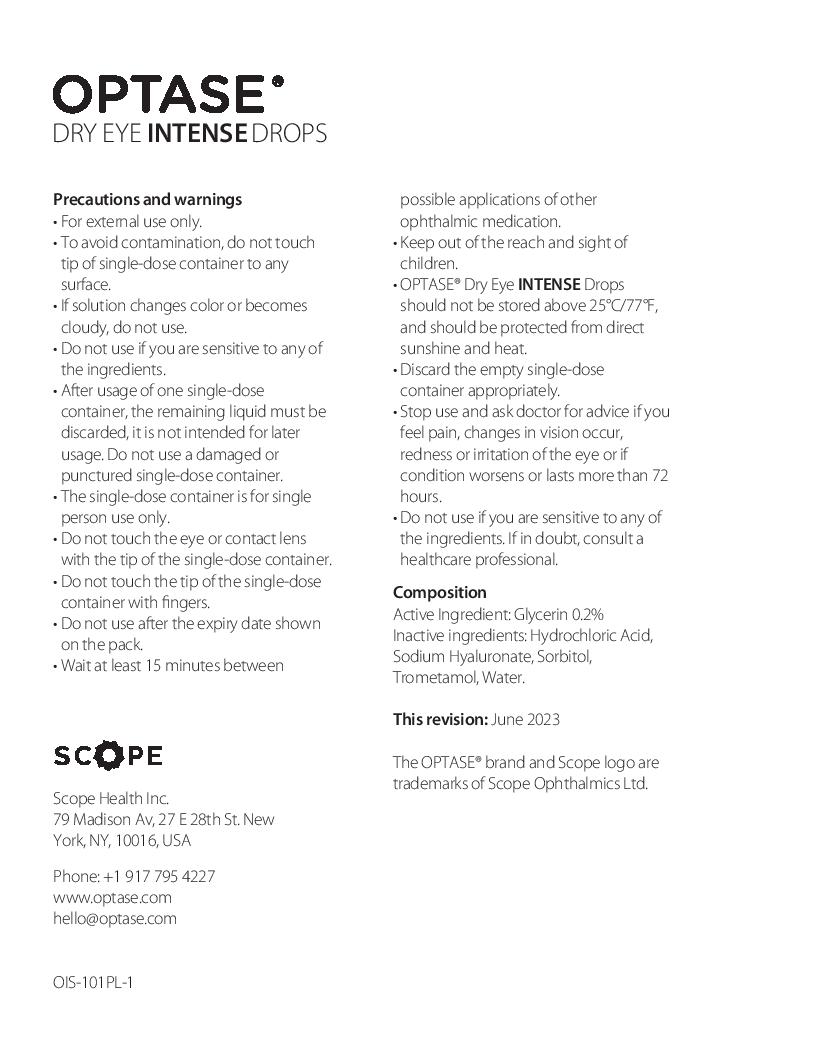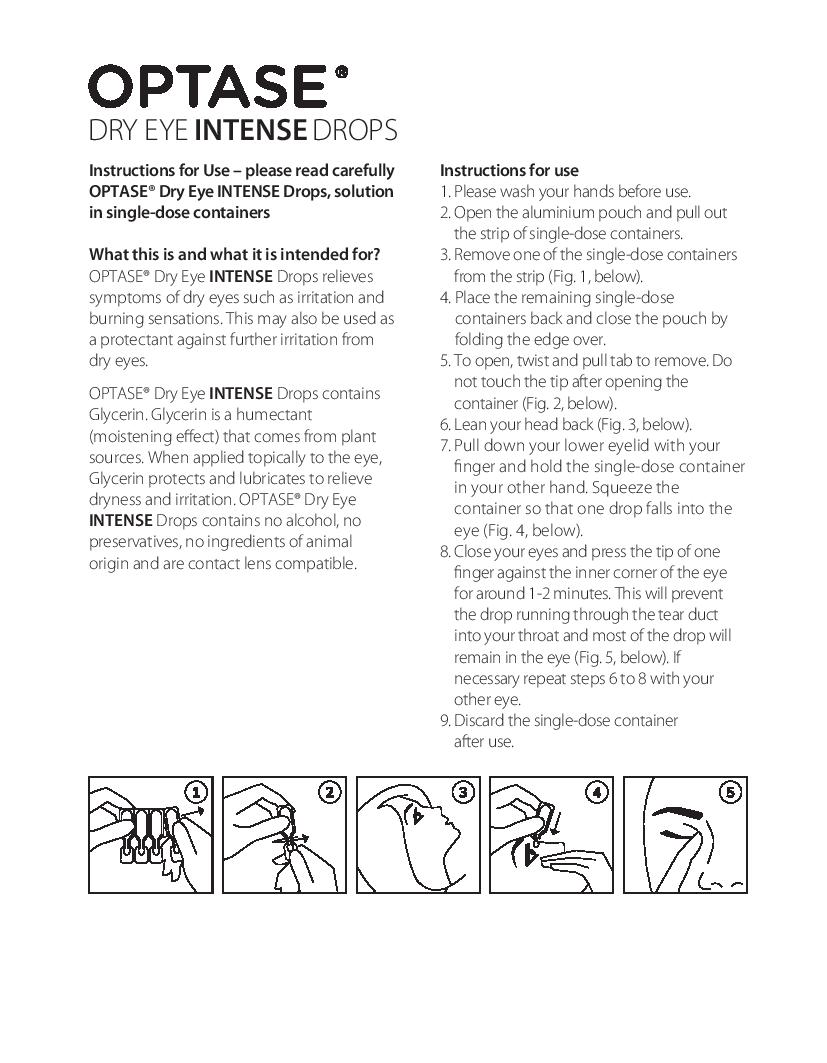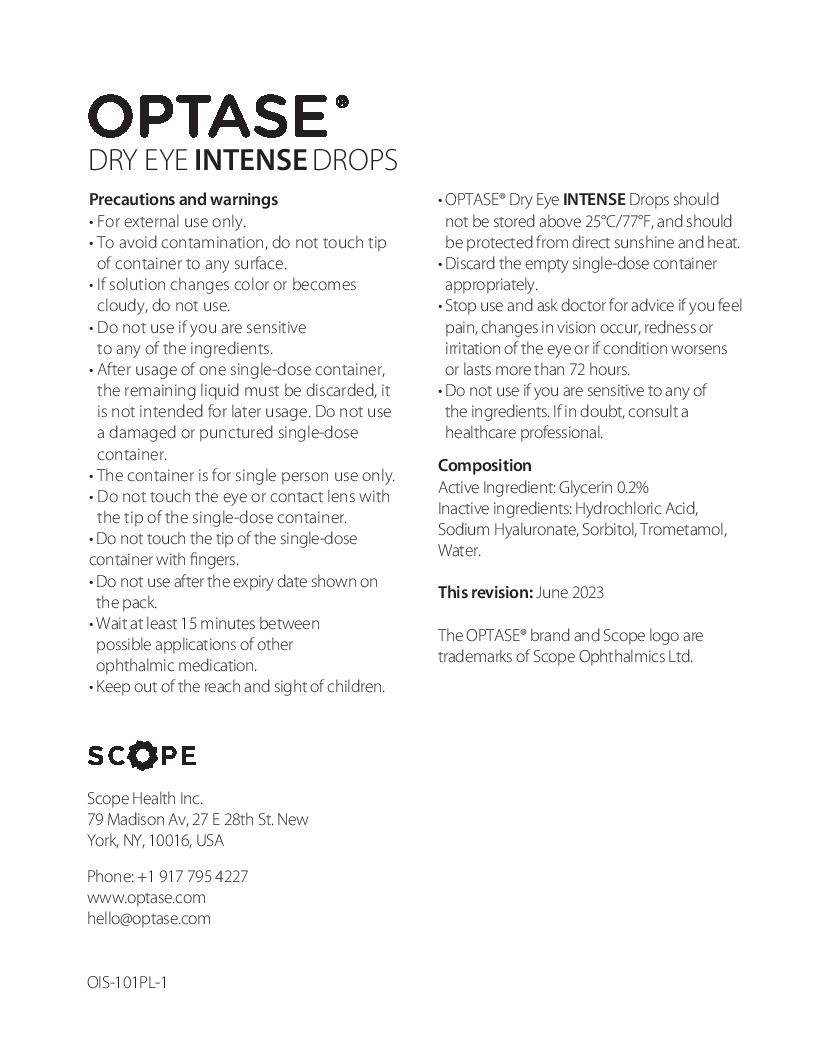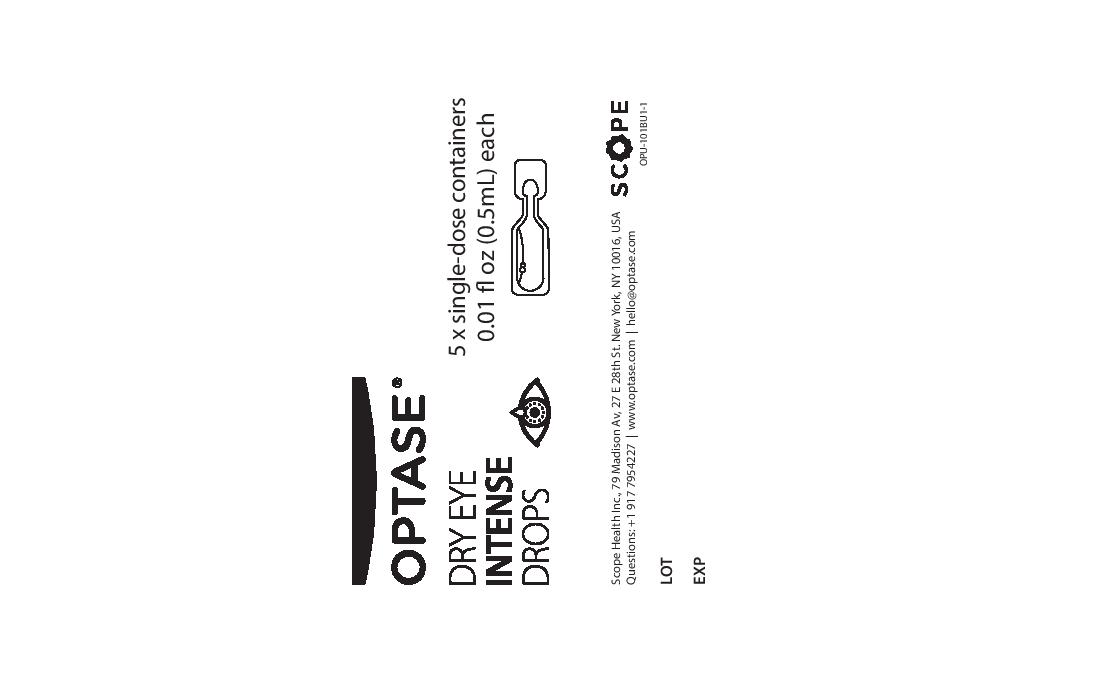 DRUG LABEL: Optase
NDC: 72972-007 | Form: SOLUTION/ DROPS
Manufacturer: Scope Health Inc
Category: otc | Type: HUMAN OTC DRUG LABEL
Date: 20260130

ACTIVE INGREDIENTS: GLYCERIN 2 mg/1 mL
INACTIVE INGREDIENTS: HYALURONATE SODIUM; HYDROCHLORIC ACID; WATER; TROMETHAMINE; SORBITOL

Optase Dry Eye Intense Drops SDU (single dose units)

ACTIVE INGREDIENT

Glycerin 0.2%

Keep out of reach of children. If swallowed get medical help or contact a poison control center right away.

PURPOSE

Eye Lubricant

Warning
• For external use only.
• To avoid contamination, do not touch tip of container to any surface.
• If solution changes color or becomes cloudy, do not use.
• Do not use a damaged or punctured single-dose container.
• Wait at least 15 minutes between possible applications of other ophthalmic medication.

• Use immediately once opened.
• Do not reuse. Discard any remaining solution after use.
• Do not use if you are sensitive to any of the ingredients.
• Do not use after the expiry date shown on the pack.

INDICATIONS AND USAGE

• For use as a lubricant to

prevent further irritation.

• May be used as a protectant

against further irritation.

•To relieve dryness of the eye.

DOSAGE AND ADMINISTRATION

• Please wash your hands before use. • Open the aluminium pouch and pull out the strip of single-dose containers. • Remove one of the single-dose containers from the strip. • Place the remaining single-dose containers back and close the pouch by folding the edge over. • To open, twist and pull tab to remove. • Do not touch the tip after opening the container. • Put one or two drops in the affected eyes as needed • Use immediately once opened. • Do not reuse. • Discard any remaining solution after use.
• No ingredients of animal origin. • Contact lens compatible.

Inactive ingredients
Hydrochloric Acid, Sodium Hyaluronate, Sorbitol, Trometamol, Water